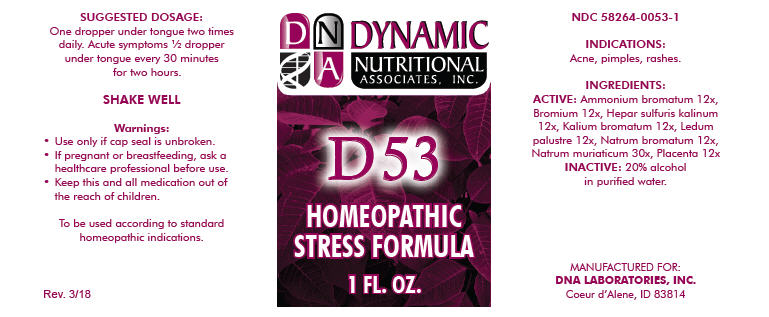 DRUG LABEL: D-53
NDC: 58264-0053 | Form: SOLUTION
Manufacturer: DNA Labs, Inc.
Category: homeopathic | Type: HUMAN OTC DRUG LABEL
Date: 20250113

ACTIVE INGREDIENTS: AMMONIUM BROMIDE 12 [hp_X]/1 mL; BROMINE 12 [hp_X]/1 mL; CALCIUM SULFIDE 12 [hp_X]/1 mL; POTASSIUM BROMIDE 12 [hp_X]/1 mL; RHODODENDRON TOMENTOSUM LEAFY TWIG 12 [hp_X]/1 mL; SODIUM BROMIDE 12 [hp_X]/1 mL; SODIUM CHLORIDE 30 [hp_X]/1 mL; BOS TAURUS PLACENTA 12 [hp_X]/1 mL
INACTIVE INGREDIENTS: ALCOHOL; WATER

D-53

NDC 58264-0053-1

INDICATIONS

PURPOSE

Acne, pimples, rashes.

INGREDIENTS

ACTIVE

Ammonium bromatum 12x, Bromium 12x, Hepar sulfuris kalinum 12x, Kalium bromatum 12x, Ledum palustre 12x, Natrum bromatum 12x, Natrum muriaticum 30x, Placenta 12x

INACTIVE

20% alcohol in purified water.

SUGGESTED DOSAGE

One dropper under tongue two times daily. Acute symptoms ½ dropper under tongue every 30 minutes for two hours.

STORAGE AND HANDLING

SHAKE WELL

Warnings

- Use only if cap seal is unbroken.

PREGNANCY OR BREAST FEEDING

- If pregnant or breastfeeding, ask a healthcare professional before use.

KEEP OUT OF REACH OF CHILDREN

- Keep this and all medication out of the reach of children.

To be used according to standard homeopathic indications.

PRINCIPAL DISPLAY PANEL - 1 FL. OZ. Bottle Label

DYNAMIC
NUTRITIONAL
ASSOCIATES, INC.

D 53

HOMEOPATHIC
STRESS FORMULA

1 FL. OZ.